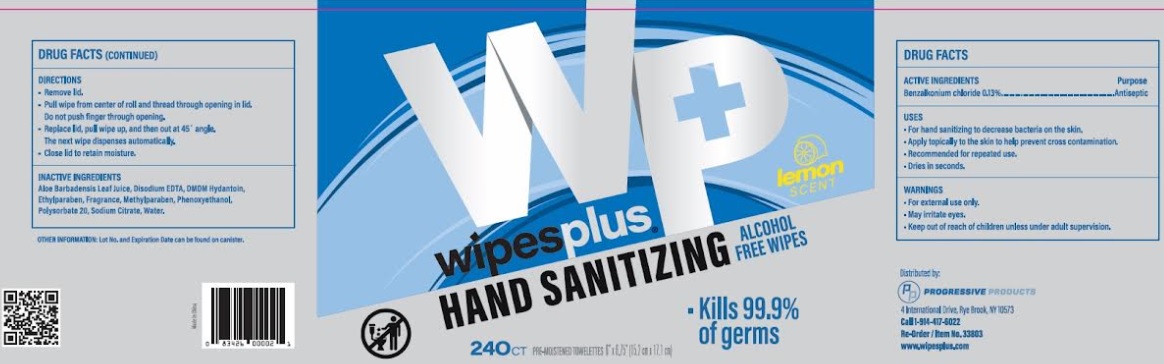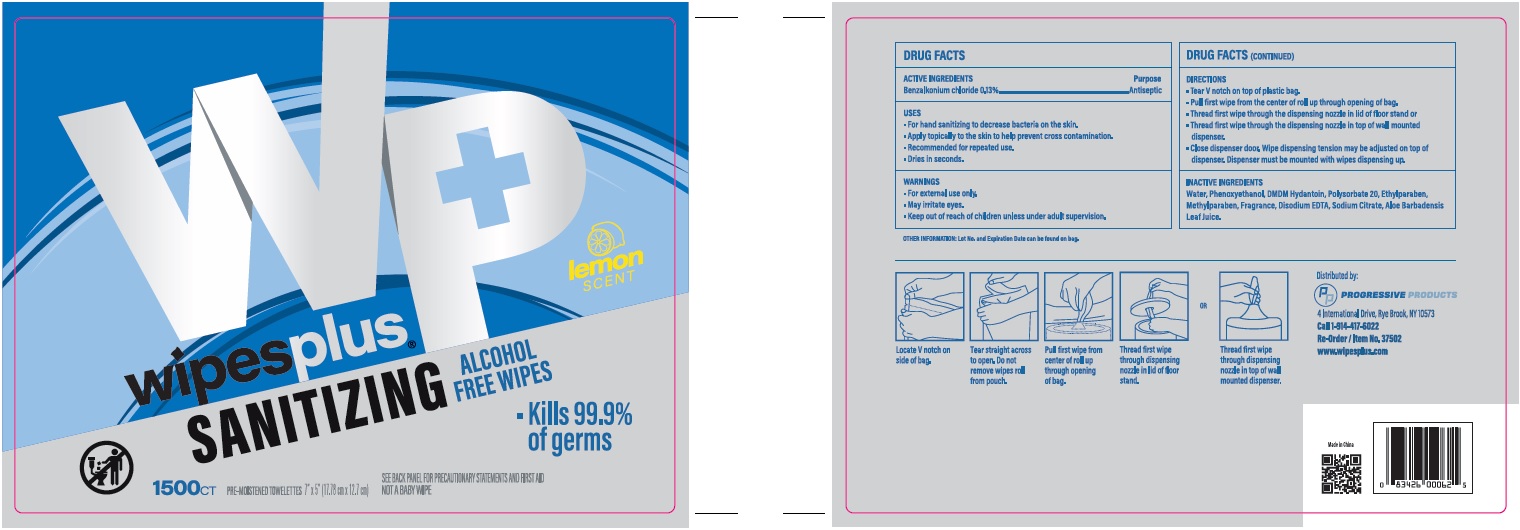 DRUG LABEL: Benzalkonium Chloride
NDC: 67151-313 | Form: CLOTH
Manufacturer: Progressive
Category: otc | Type: HUMAN OTC DRUG LABEL
Date: 20221014

ACTIVE INGREDIENTS: BENZALKONIUM CHLORIDE 0.0013 mg/100 mg
INACTIVE INGREDIENTS: ETHYLPARABEN; SODIUM CITRATE; EDETATE DISODIUM ANHYDROUS; PHENOXYETHANOL; DMDM HYDANTOIN; POLYSORBATE 20; METHYLPARABEN; ALOE VERA LEAF; WATER

Hand Sanitizing Wipes

Active ingredients

Benzalkonium Chloride 0.13%

Purpose

Antiseptic

Uses

- For hand sanitizing to decrease bacteria on the skin
- Apply topically to the skin to help prevent cross contamination
- Recommended for repeated use
- Dries in seconds

Warnings

For external use only.

May irritate eyes.

Keep out of reach of children unless under adult supervision

Directions

- Remove lid
- Pull wipe from center of roll and thread through opening in lid

Do not push finger through opening

- Replace lid, pull wipe up, and then out 45º angle

The next wipe dispenses automatically

- Close lid to retain moisture

Inactive ingredient

Aloe Barbadensis Leaf Juice, Disodium EDTA, DMDM Hydantoin, Ethylparaben, Fragrance, Methylparaben, Phenoxyethanol, Polysorbate 20, Sodium Citrate, Water

Principal Display Panel

wipesplus

HAND SANITIZING

alcohol wipes

lemon scent

Kills 99.9% of germs